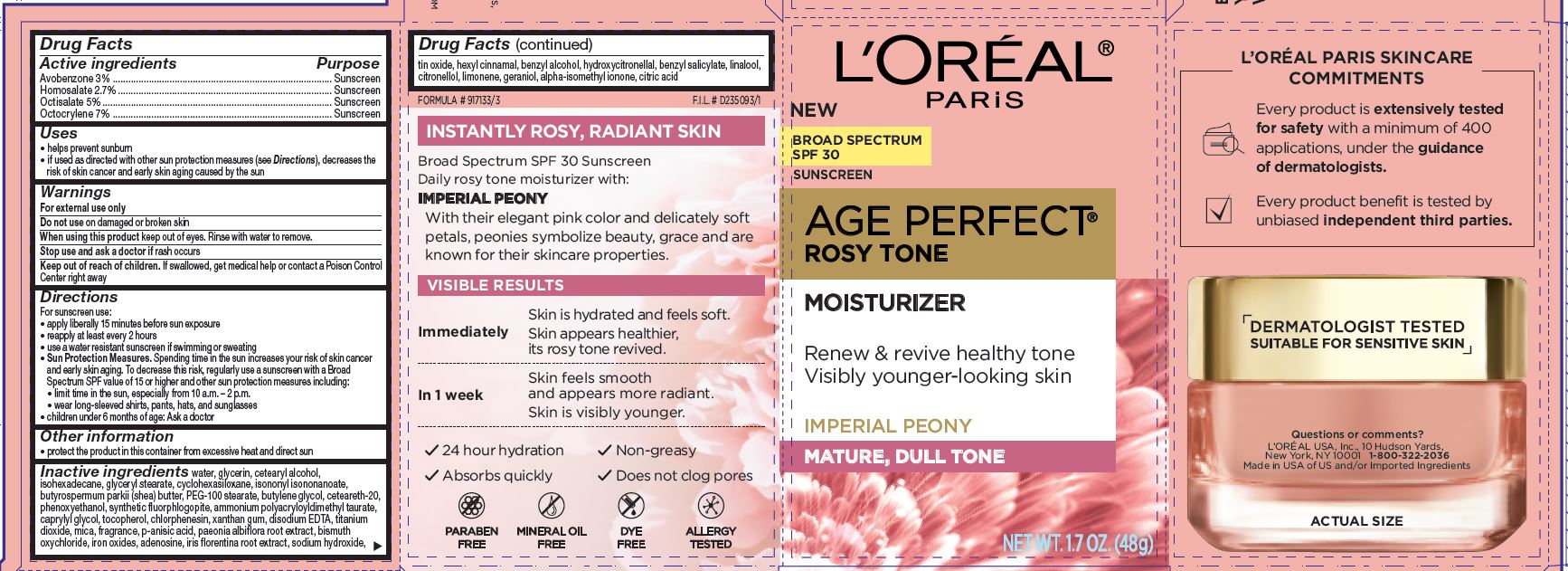 DRUG LABEL: Loreal Paris Age Perfect Rosy Tone SPF 30 Renew and revive healthy tone Visibly younger-looking skin
NDC: 49967-394 | Form: LOTION
Manufacturer: L'Oreal USA Products Inc
Category: otc | Type: HUMAN OTC DRUG LABEL
Date: 20231229

ACTIVE INGREDIENTS: AVOBENZONE 30 mg/1 mL; HOMOSALATE 27 mg/1 mL; OCTISALATE 50 mg/1 mL; OCTOCRYLENE 50 mg/1 mL
INACTIVE INGREDIENTS: WATER; GLYCERIN; CETOSTEARYL ALCOHOL; CYCLOMETHICONE 6; ISONONYL ISONONANOATE; ISOHEXADECANE; GLYCERYL MONOSTEARATE; SHEA BUTTER; PEG-100 STEARATE; BUTYLENE GLYCOL; POLYOXYL 20 CETOSTEARYL ETHER; PHENOXYETHANOL; AMMONIUM POLYACRYLOYLDIMETHYL TAURATE (55000 MPA.S); caprylyl glycol; TOCOPHEROL; CHLORPHENESIN; XANTHAN GUM; EDETATE DISODIUM; TITANIUM DIOXIDE; MICA; P-ANISIC ACID; PAEONIA LACTIFLORA ROOT; BISMUTH OXYCHLORIDE; FERRIC OXIDE RED; ADENOSINE; IRIS X GERMANICA NOTHOVAR. FLORENTINA ROOT; SODIUM HYDROXIDE; STANNIC OXIDE; .ALPHA.-HEXYLCINNAMALDEHYDE; BENZYL ALCOHOL; HYDROXYCITRONELLAL; BENZYL SALICYLATE; LINALOOL, (+/-)-; .BETA.-CITRONELLOL, (R)-; LIMONENE, (+)-; GERANIOL; ISOMETHYL-.ALPHA.-IONONE; CITRIC ACID MONOHYDRATE

Drug Facts

Active ingredients

Avobenzone 3%

Homosalate 2.7%

Octisalate 5%

Octocrylene 7%

Purpose

Sunscreen

Uses

- helps prevent sunburn
- if used as directed with other sun protection measures (see Directions), decreases the risk of skin cancer and early skin aging caused by the sun

Warnings

For external use only

Do not use

on damaged or broken skin

When using this product

keep out of eyes. Rinse with water to remove.

Stop use and ask a doctor if

rash occurs

Keep out of reach of children.

If swallowed, get medical help or contact a Poison Control Center right away

Directions

For sunscreen use:

- apply liberally 15 minutes before sun exposure
- reapply at least every 2 hours
- use a water resistant suncreen if swimming or sweating
- Sun Protection Measures. Spending time in the sun increases your risk of skin cancer and early skin aging. To decrease this risk, regularly use a sunscreen with a Broad Spectrum SPF value of 15 or higher and other sun protection measures including:
- limit time in the sun, especially from 10 a.m. - 2 p.m.
- wear long-sleeved shrits, pants, hat and sunglasses
- children under 6 months of age: Ask a doctor

Other information

- protect the product in this container from excessive heat and direct sun

Inactive ingredients

water, glycerin, cetearyl alcohol, isohexadecane, glyceryl stearate, cyclohexasiloxane, isononyl isononanoate, butyrospermum parkii (shea) butter, PEG-100 stearate, butylene glycol, ceteareth-20, phenoxyethanol, synthetic fluorphlogopite, ammonium polyacryloyldimethyl taurate, caprylyl glycol, tocopherol, chlorphenesin, xanthan gum, disodium EDTA, titanium dioxide, mica, fragrance, p-anisic acid, paeonia albiflora root extract, bismuth oxychloride, iron oxides, adenosine, iris florentina root extract, sodium hydroxide, tin oxide, hexyl cinnamal, benzyl alcohol, hydroxycitrinellal, benzyl salicylate, linalool, citronellol, limonene, geraniol, alpha-isomethyl ionone, citric acid